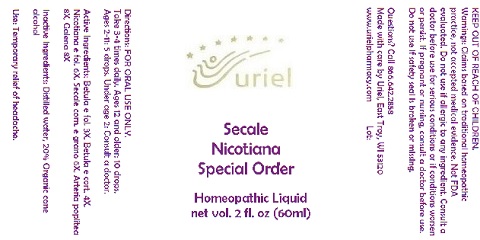 DRUG LABEL: Secale Nicotiana Special Order
NDC: 48951-8289 | Form: LIQUID
Manufacturer: Uriel Pharmacy Inc.
Category: homeopathic | Type: HUMAN OTC DRUG LABEL
Date: 20180501

ACTIVE INGREDIENTS: BETULA PUBESCENS LEAF 3 [hp_X]/1 mL; BETULA PUBESCENS BARK 4 [hp_X]/1 mL; TOBACCO LEAF 6 [hp_X]/1 mL; CLAVICEPS PURPUREA SCLEROTIUM 6 [hp_X]/1 mL; BOS TAURUS ARTERY 8 [hp_X]/1 mL; LEAD SULFIDE 8 [hp_X]/1 mL
INACTIVE INGREDIENTS: WATER; ALCOHOL

Secale Nicotiana Special Order

INDICATIONS AND USAGE

Directions: FOR ORAL USE ONLY.

DOSAGE AND ADMINISTRATION

Take 3-4 times daily. Ages 12 and older: 10 drops. Ages 2-11: 5 drops. Under age 2: Consult a doctor.

ACTIVE INGREDIENT

Active Ingredients: Betula e fol. 3X, Betula e cort. 4X, Nicotiana e fol. 6X, Secale corn. e grano 6X, Arteria poplitea 8X, Galena 8X

Inactive Ingredients: Distilled water, 20% Organic cane alcohol

PURPOSE

Use: Temporary relief of headache.

KEEP OUT OF REACH OF CHILDREN.

WARNINGS

Warnings: Claims based on traditional homeopathic practice, not accepted medical evidence. Not FDA evaluated. Do not use if allergic to any ingredient. Consult a doctor before use for serious conditions or if conditions worsen or persist. If pregnant or nursing, consult a doctor before use. Do not use if safety seal is broken or missing.

QUESTIONS

Questions? Call 866.642.2858 Made with care by Uriel, East Troy, WI 53120 www.urielpharmacy.com